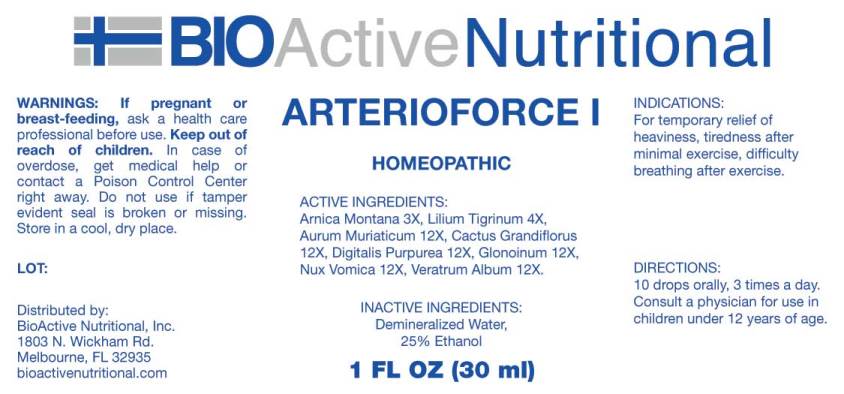 DRUG LABEL: Arterioforce
NDC: 43857-0159 | Form: LIQUID
Manufacturer: BioActive Nutritional, Inc.
Category: homeopathic | Type: HUMAN OTC DRUG LABEL
Date: 20250516

ACTIVE INGREDIENTS: ARNICA MONTANA 3 [hp_X]/1 mL; LILIUM LANCIFOLIUM WHOLE FLOWERING 4 [hp_X]/1 mL; GOLD TRICHLORIDE 12 [hp_X]/1 mL; SELENICEREUS GRANDIFLORUS STEM 12 [hp_X]/1 mL; DIGITALIS 12 [hp_X]/1 mL; NITROGLYCERIN 12 [hp_X]/1 mL; STRYCHNOS NUX-VOMICA SEED 12 [hp_X]/1 mL; VERATRUM ALBUM ROOT 12 [hp_X]/1 mL
INACTIVE INGREDIENTS: WATER; ALCOHOL

Drug Facts:

ACTIVE INGREDIENTS:

Arnica Montana 3X, Lilium Tigrinum 4X, Aurum Muriaticum 12X, Cactus Grandiflorus 12X, Digitalis Purpurea 12X, Glonoinum 12X, Nux Vomica 12X, Veratrum Album 12X.

INDICATIONS:

For temporary relief of heaviness, tiredness after minimal exercise, difficulty breathing after exercise.

WARNINGS:

If pregnant or breast-feeding, ask a health care professional before use.

Keep out of reach of children. In case of overdose, get medical help or contact a Poison Control Center right away.

Do not use if tamper evident seal is broken or missing.

Store in cool, dry place.

DIRECTIONS:

10 drops orally, 3 times a day. Consult a physician for use in children under 12 years of age.

INACTIVE INGREDIENTS:

Demineralized Water, 25% Ethanol.

Keep out of reach of children. In case of overdose, get medical help or contact a Poison Control Center right away.

INDICATIONS:

For temporary relief of heaviness, tiredness after minimal exercise, difficulty breathing after exercise.

QUESTIONS:

Distributed by:

BioActive Nutritional, Inc.

1803 N. Wickham Rd.

Melbourne, FL 32935

bioactivenutritional.com

PACKAGE LABEL DISPLAY:

BIOActive Nutritional

ARTERIOFORCE I

HOMEOPATHIC

1 FL OZ (30 ml)